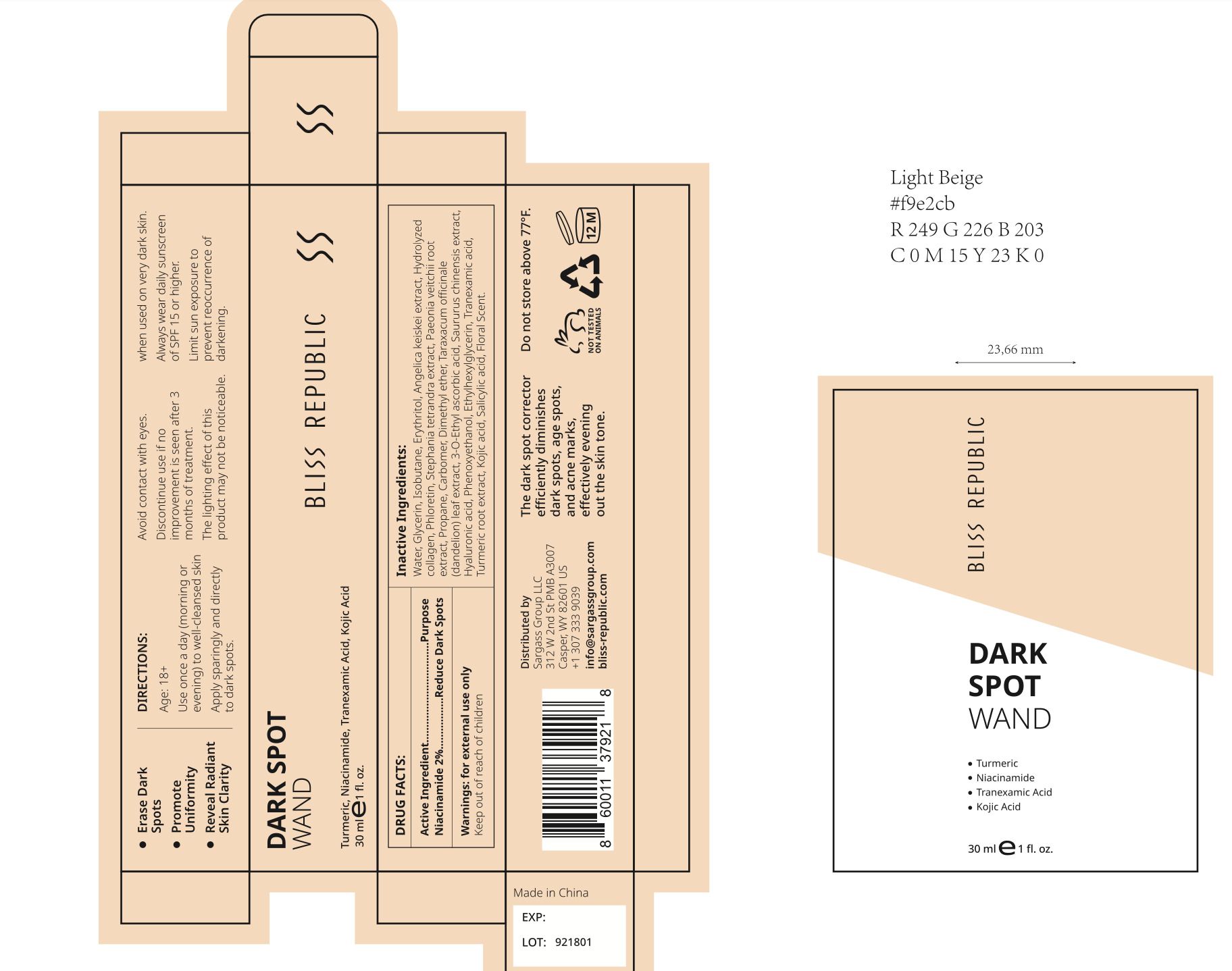 DRUG LABEL: Bliss Republic Dark Spot Wand
NDC: 84028-112 | Form: SOLUTION
Manufacturer: Sargass Group Limited Liability Company
Category: otc | Type: HUMAN OTC DRUG LABEL
Date: 20240216

ACTIVE INGREDIENTS: NIACINAMIDE 2 mg/100 mL
INACTIVE INGREDIENTS: CARBOMER HOMOPOLYMER, UNSPECIFIED TYPE; PROPANE; TURMERIC; 3-O-ETHYL ASCORBIC ACID; PAEONIA VEITCHII ROOT; PHLORETIN; STEPHANIA TETRANDRA ROOT; PHENOXYETHANOL; TRANEXAMIC ACID; GLYCERIN; ISOBUTANE; ANGELICA KEISKEI ROOT; SAURURUS CHINENSIS FLOWER; ETHYLHEXYLGLYCERIN; KOJIC ACID; DIMETHYL ETHER; TARAXACUM OFFICINALE LEAF; SALICYLIC ACID; HYALURONIC ACID; HYDROLYSED MARINE COLLAGEN (ENZYMATIC; 2000 MW); ERYTHRITOL; WATER

BLISS REPUBLIC Dark Spot Wand

Active Ingredient(s)

Niacinamide 2%................. Reduce Dark Spots

Purpose

Reduce Dark Spots

Use

To reduce Dark Spots on the skin

Warnings

For external use only

WHEN USING

Avoid contact with eyes.

KEEP OUT OF REACH OF CHILDREN

Keep away from children. Avoid contact with eyes. In case of accidental ingestion, seek medical attention immefiately.

STOP USE

Discontinue use if no improvement is seen after 3 months of treatment.

Directions

Age: 18+ Use once a day (morning or

evening) to well-cleansed skin

Apply sparingly and directly

to dark spots.

Other information

Always wear daily sunscreen of SPF 15 or higher when used on very dark skin.

The lighting effect of this product may not be noticeable.

Limit sun exposure to prevent reoccurrence of darkening.

Inactive ingredients

Water, Glycerin, Isobutane, Erythritol, Angelica keiskei extract, Hydrolyzed

collagen, Phloretin, Stephania tetrandra extract, Paeonia veitchii root extract, Propane, Carbomer, Dimethyl ether, Taraxacum officinale

(dandelion) leaf extract, 3-0-Ethyl ascorbic acid, Saururus chinensis extract,

Hyaluronic acid, Phenoxyethanol, Ethylhexylglycerin, Tranexamic acid,

Turmeric root extract, Kojic acid, Salicylic acid, Floral Scent.

RECENT MAJOR CHANGES

BLISS REPUBLIC DARK SPOT WAND

Turmeric, Niacinamide, Tranexamic Acid, Kojic Acid

Erase DarkSpots
Promote Uniformity
Reveal Radiant Skin Clarity

Customer Care:

For any questions, please contact us for a quick and satisfactory solution:

info@sargassgroup.com

Distributed by Sargass Group LLC, Casper, WY 82601

312 W 2nd St, A3007

+1 307 333 9039

Package Label - Principal Display Panel

30mL NDC: 84028-112-11